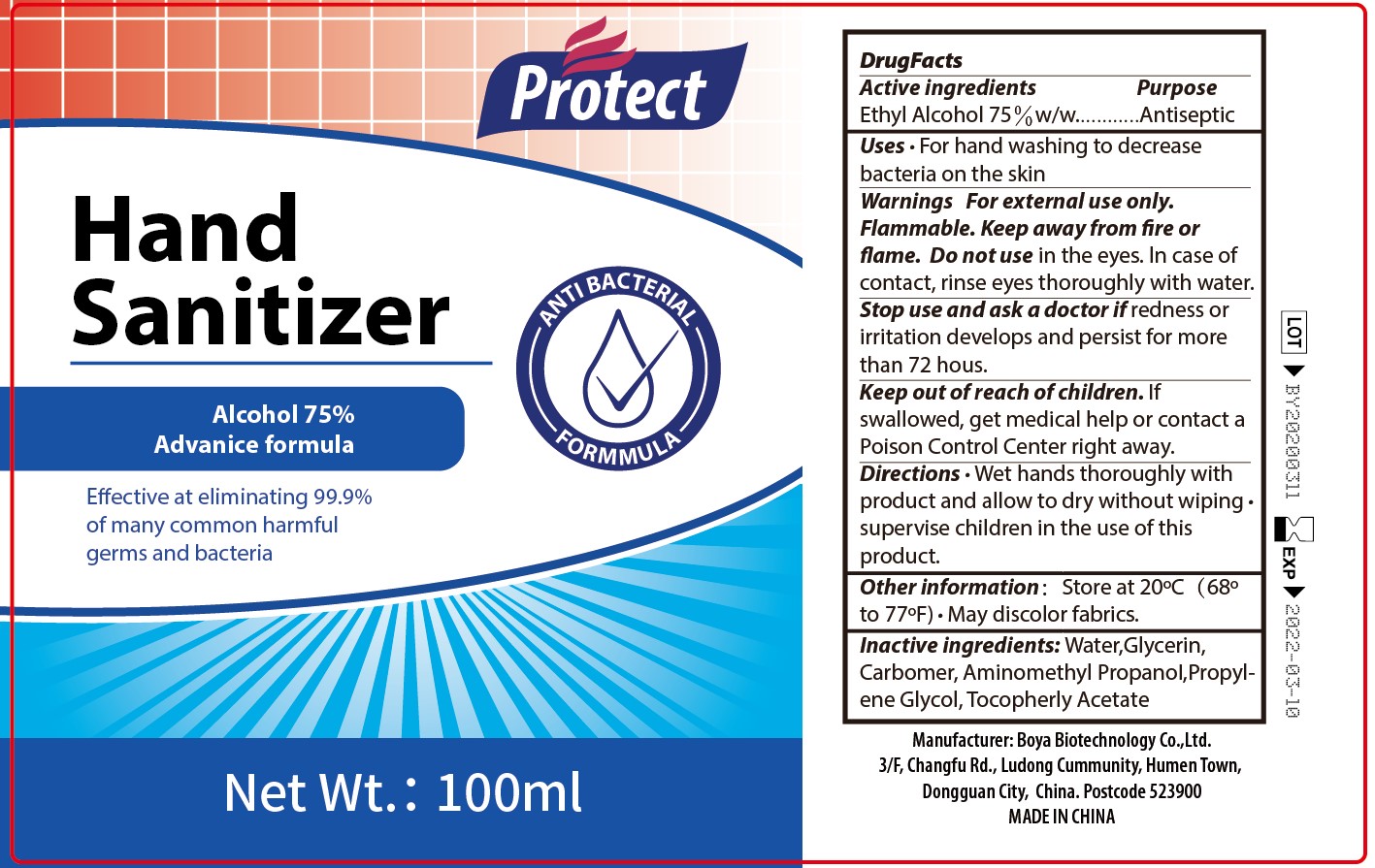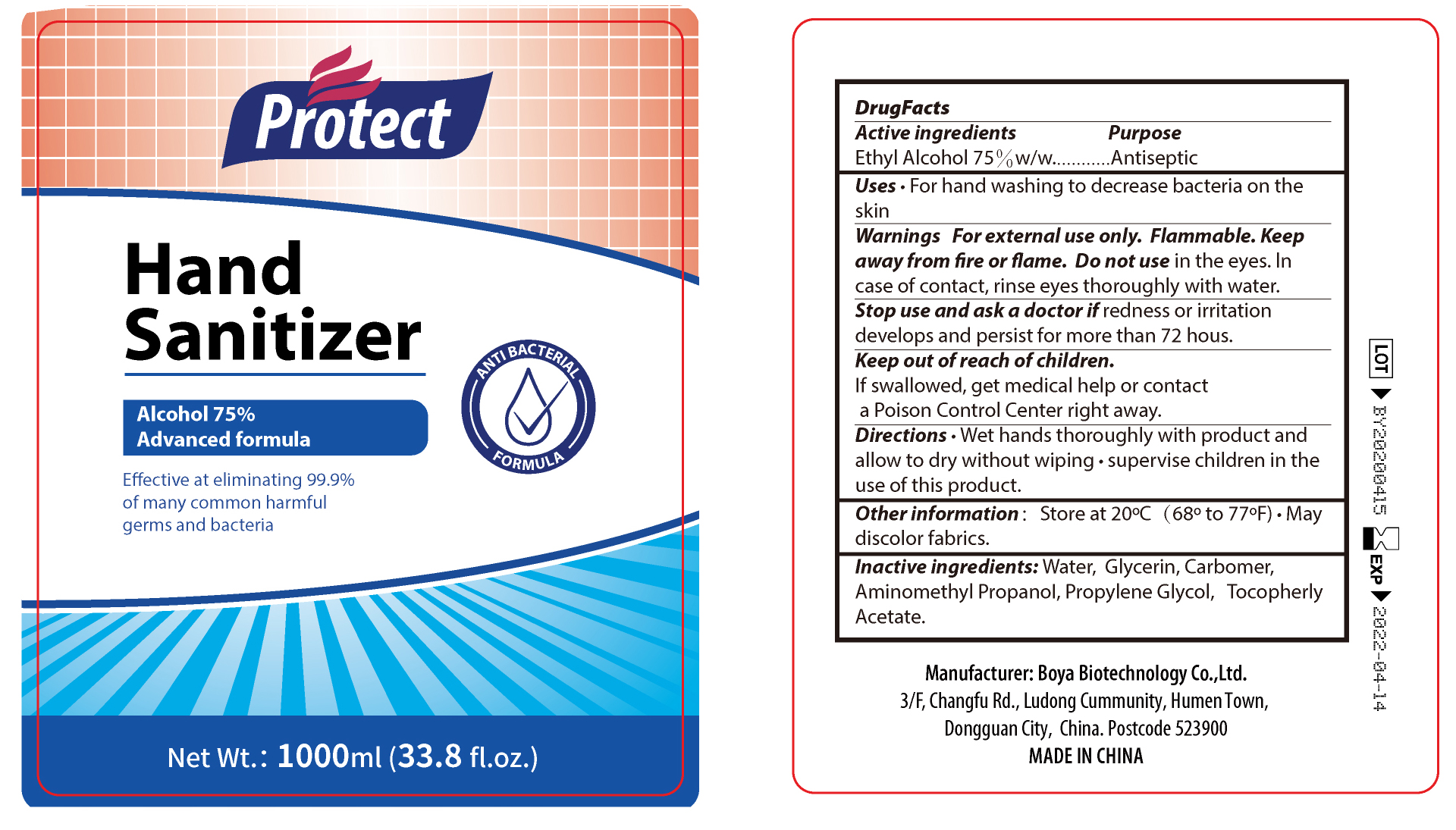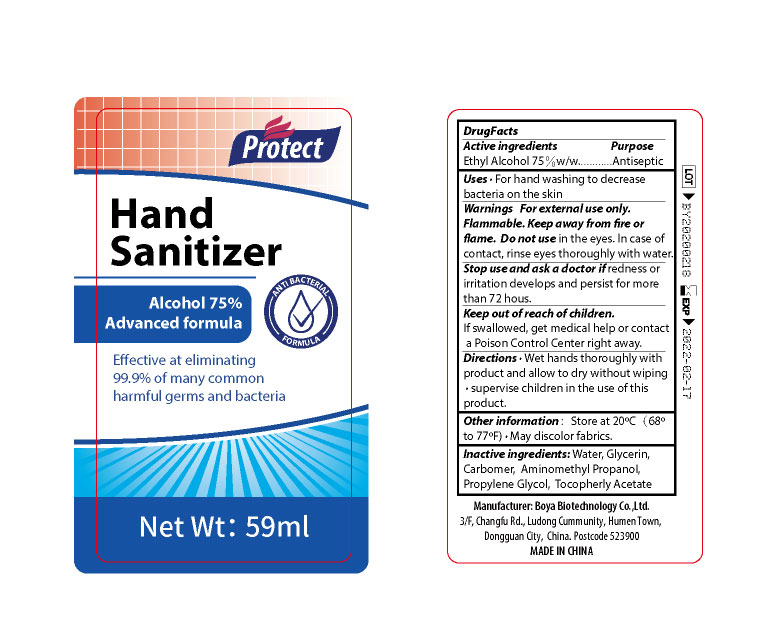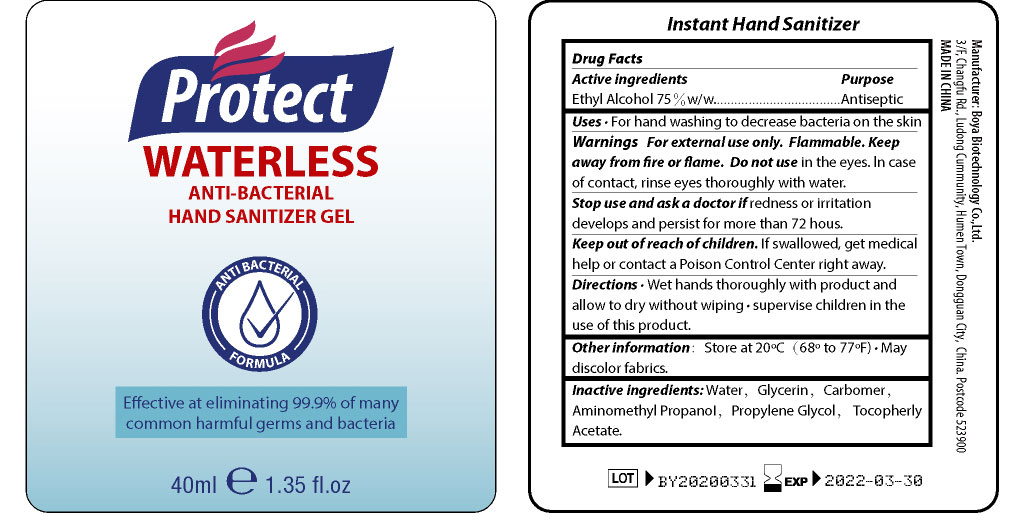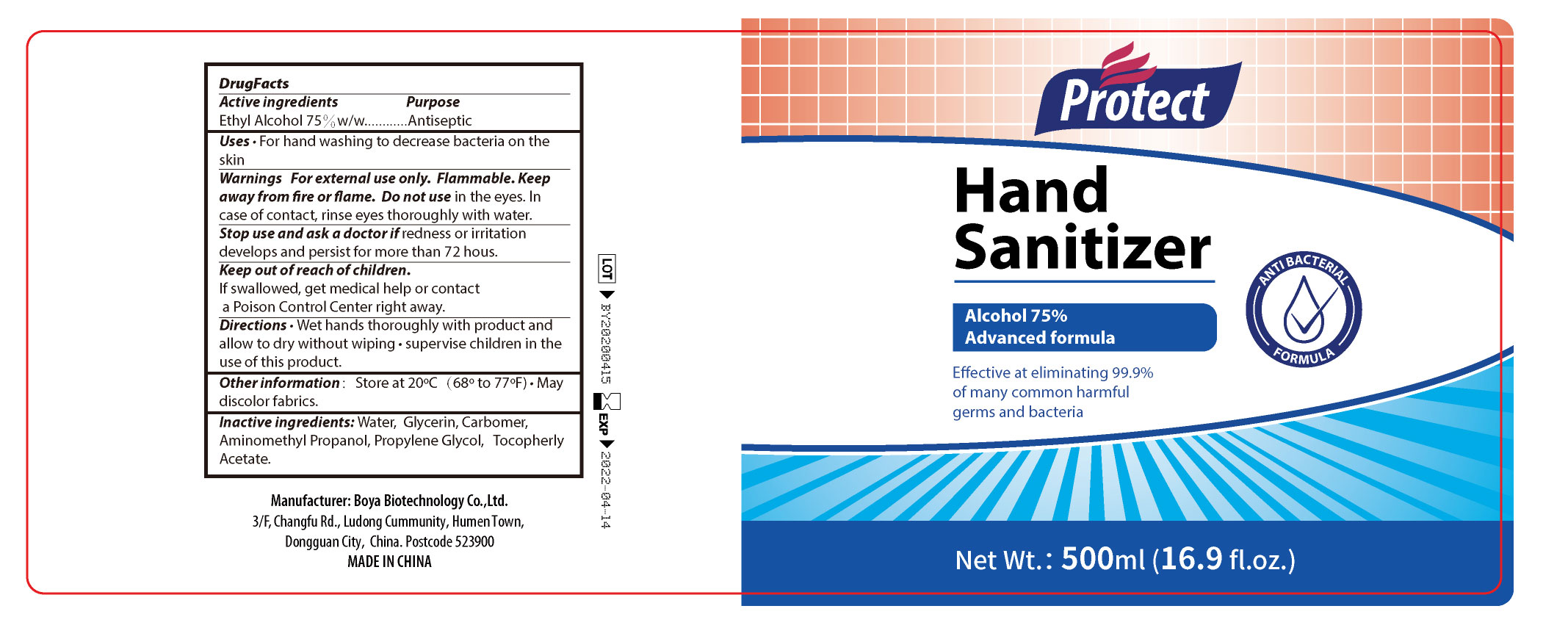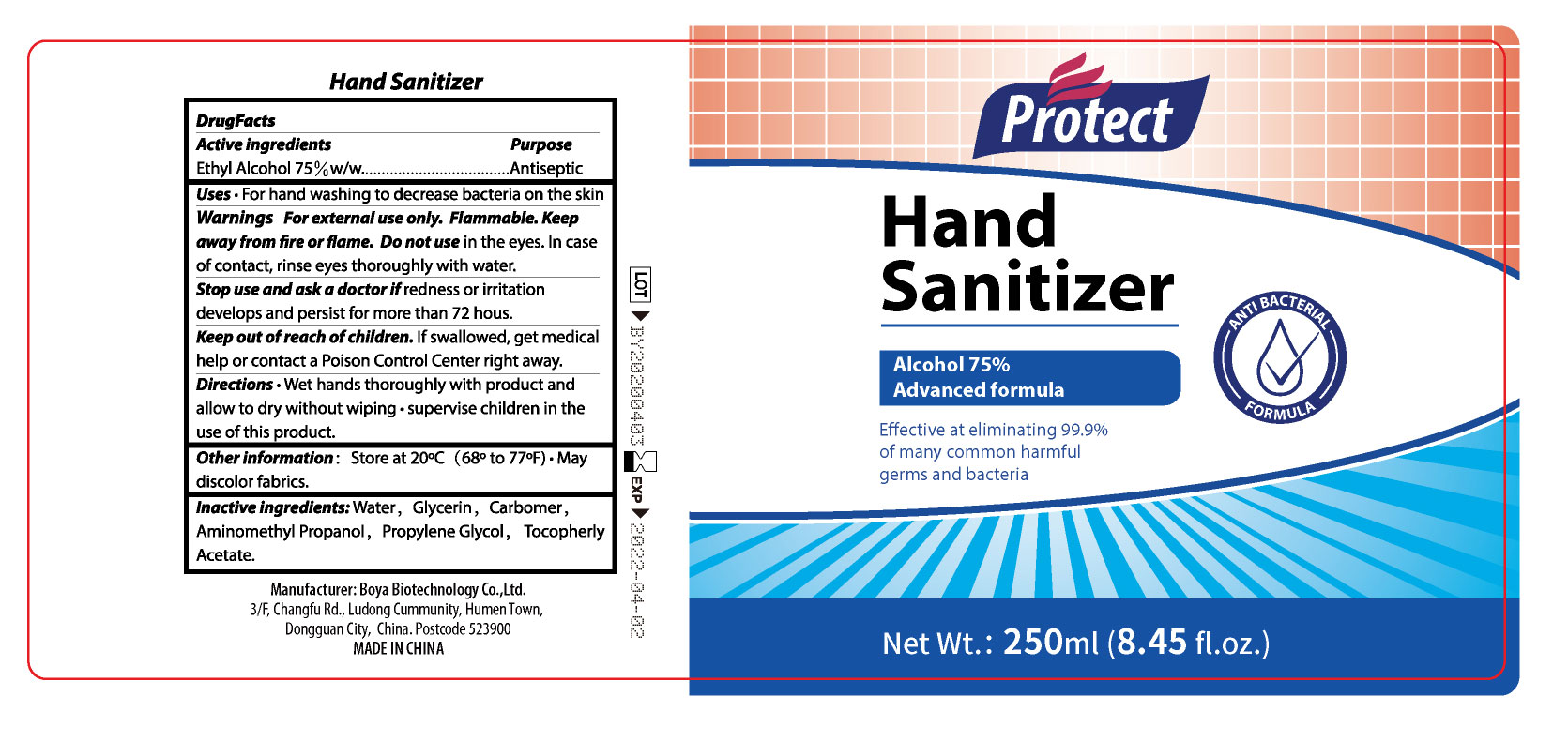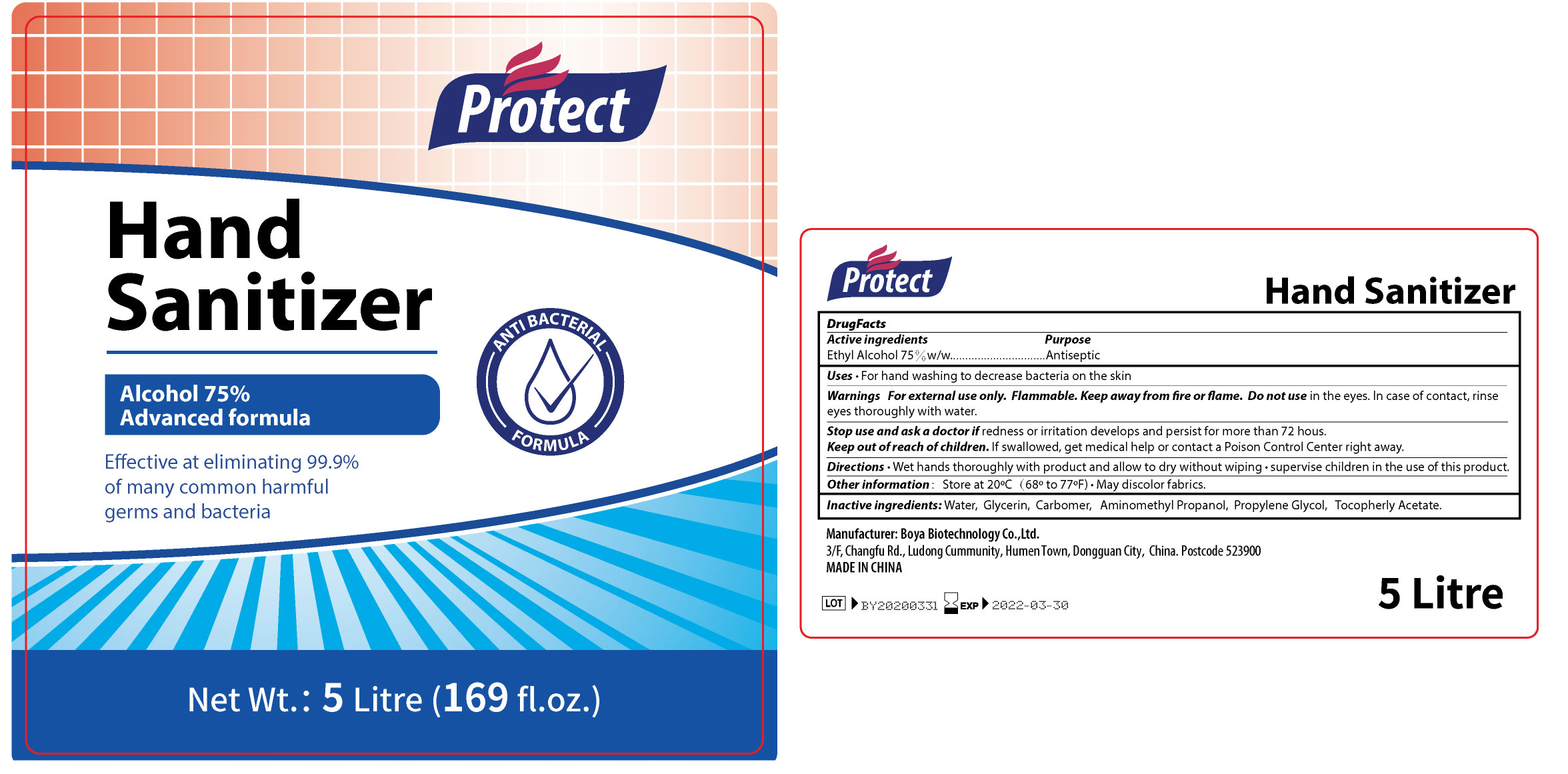 DRUG LABEL: Protect Hand Sanitizer
NDC: 73885-001 | Form: SOLUTION
Manufacturer: Boya Biotechnology Company Limited
Category: otc | Type: HUMAN OTC DRUG LABEL
Date: 20200426

ACTIVE INGREDIENTS: ALCOHOL 75 mL/100 mL
INACTIVE INGREDIENTS: GLYCERIN; CARBOMER 934; WATER; PROPYLENE GLYCOL; .ALPHA.-TOCOPHEROL ACETATE; AMINOMETHYL PROPANEDIOL

Active Ingredient(s)

Alcohol 75% v/v. Purpose: Antiseptic

Purpose

Antiseptic

Use

For hand washing to decrease bacteria on the skin

Warnings

For external use only. Flammable. Keep away from fire or flame

Do not use in the eyes. In case of contatc, rinse eyes thoroughly with water.

When using this product keep out of eyes, ears, and mouth. In case of contact with eyes, rinse eyes thoroughly with water.
Stop use and ask a doctor if irritation or rash occurs. These may be signs of a serious condition.
Keep out of reach of children. If swallowed, get medical help or contact a Poison Control Center right away.

Stop use and ask a doctor if redness or irritation develops and persist for more than 72 hours

Keep out of reach of children. If swallowed, get medical help or contact a Poison Control Center right away.

Directions

- Wash hands thoroughly with product and allow to dry without wiping.
- Supervise children in the use of this product to avoid swallowing.

Other information

- Store between 15-30C (59-86F)
- May discolor fabrics

Inactive ingredients

Water, Glycerin, Carbomer, Aminomethyl Propanol, Propylene Glycol, Tocopherol Acetate